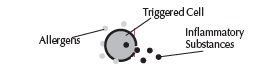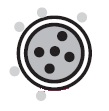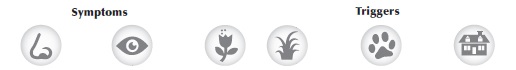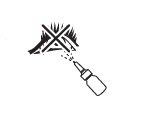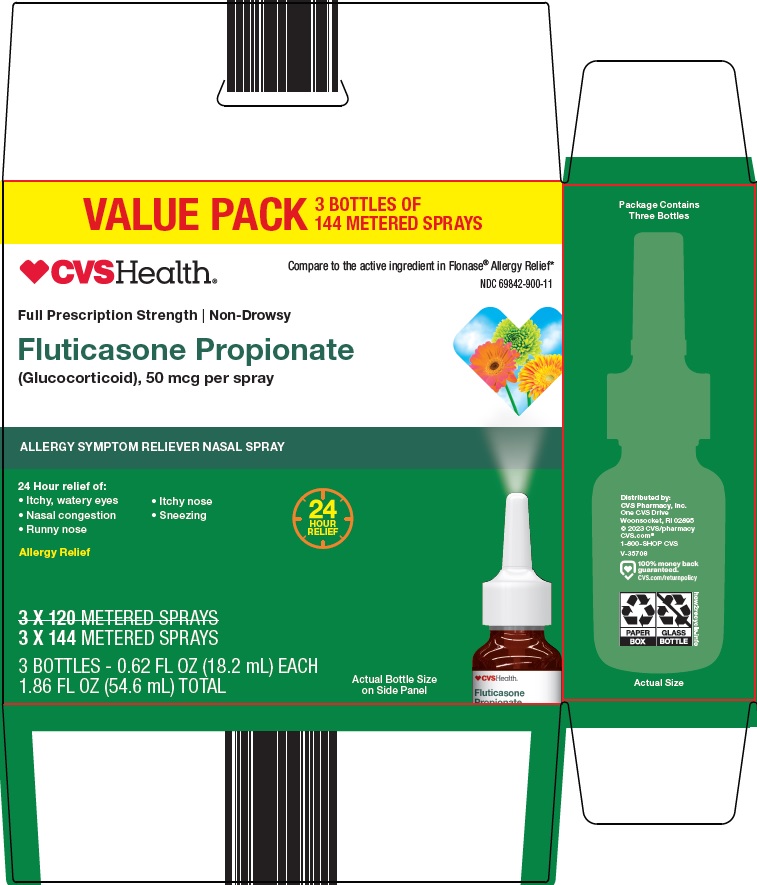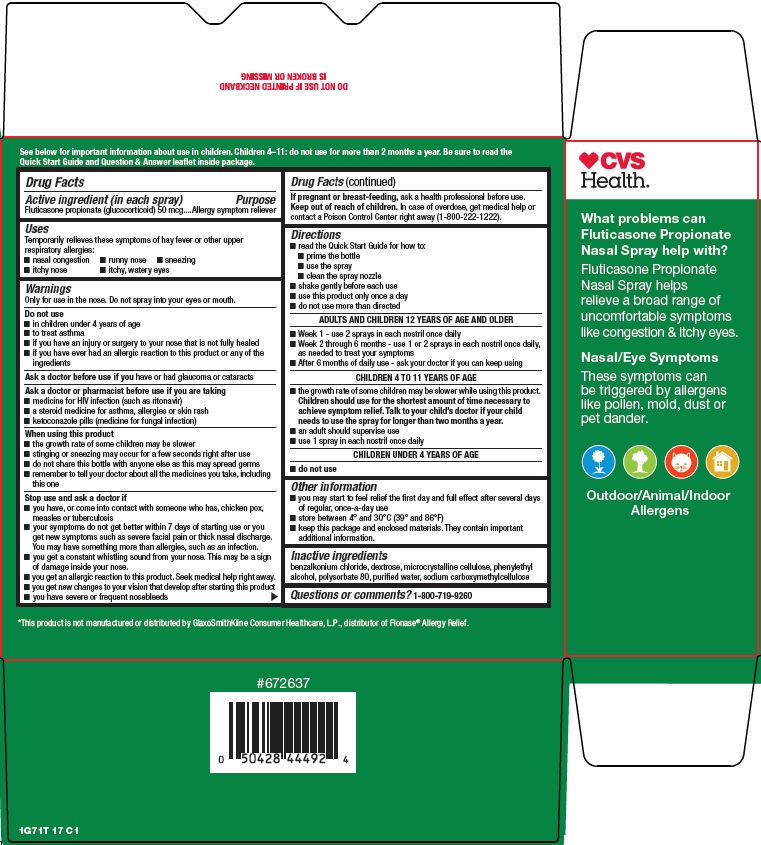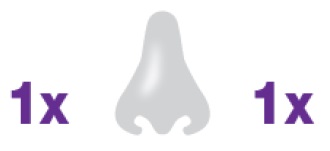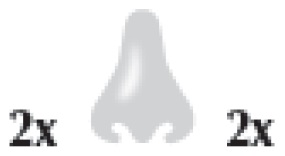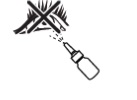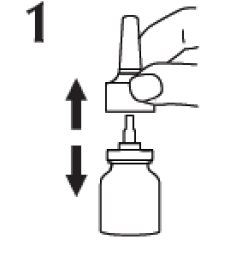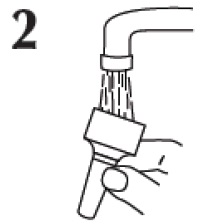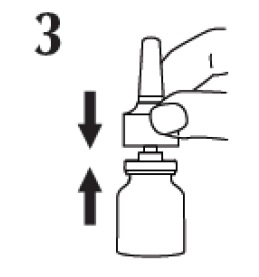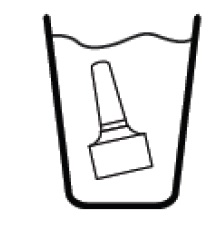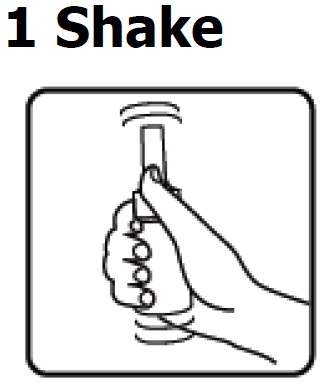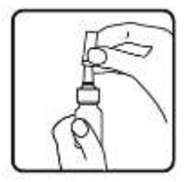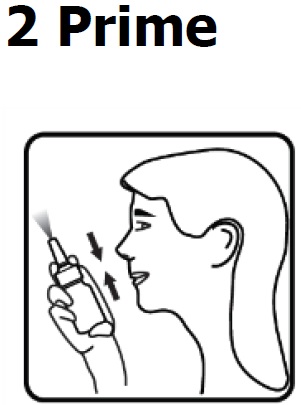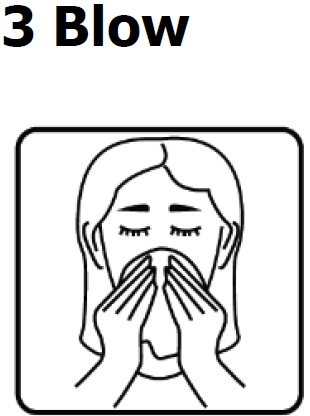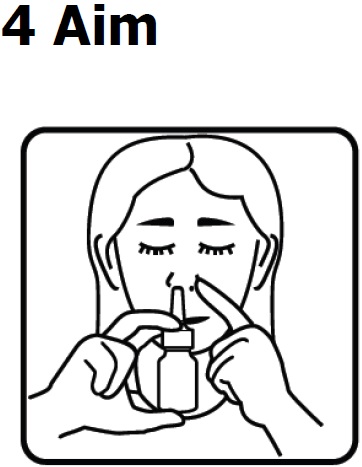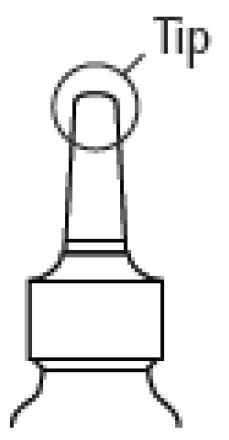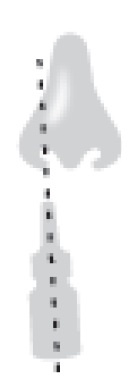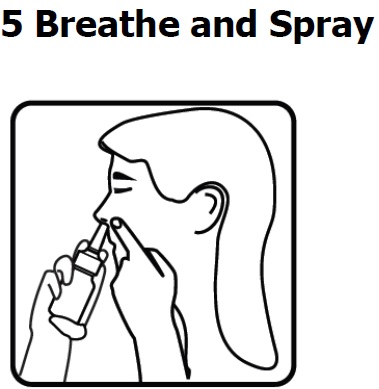 DRUG LABEL: Fluticasone Propionate Nasal
NDC: 69842-900 | Form: SPRAY, METERED
Manufacturer: CVS Pharmacy
Category: otc | Type: HUMAN OTC DRUG LABEL
Date: 20260226

ACTIVE INGREDIENTS: FLUTICASONE PROPIONATE 50 ug/1 1
INACTIVE INGREDIENTS: BENZALKONIUM CHLORIDE; DEXTROSE, UNSPECIFIED FORM; MICROCRYSTALLINE CELLULOSE; PHENYLETHYL ALCOHOL; POLYSORBATE 80; WATER; CARBOXYMETHYLCELLULOSE SODIUM, UNSPECIFIED

CVS Pharmacy, Inc. Fluticasone Propionate Drug Facts

Active ingredient (in each spray)

Fluticasone propionate (glucocorticoid) 50 mcg

Purpose

Allergy symptom reliever

Uses

Temporarily relieves these symptoms of hay fever or other upper respiratory allergies:

- nasal congestion
- runny nose
- sneezing
- itchy nose
- itchy, watery eyes

Warnings

Only for use in the nose. Do not spray into your eyes or mouth.

Do not use

- in children under 4 years of age
- to treat asthma
- if you have an injury or surgery to your nose that is not fully healed
- if you have ever had an allergic reaction to this product or any of the ingredients

Ask a doctor before use if you

have or had glaucoma or cataracts

Ask a doctor or pharmacist before use if you are taking

- medicine for HIV infection (such as ritonavir)
- a steroid medicine for asthma, allergies or skin rash
- ketoconazole pills (medicine for fungal infection)

When using this product

- the growth rate of some children may be slower
- stinging or sneezing may occur for a few seconds right after use
- do not share this bottle with anyone else as this may spread germs
- remember to tell your doctor about all the medicines you take, including this one

Stop use and ask a doctor if

- you have, or come into contact with someone who has, chicken pox, measles or tuberculosis
- your symptoms do not get better within 7 days of starting use or you get new symptoms such as severe facial pain or thick nasal discharge. You may have something more than allergies, such as an infection.
- you get a constant whistling sound from your nose. This may be a sign of damage inside your nose.
- you get an allergic reaction to this product. Seek medical help right away.
- you get new changes to your vision that develop after starting this product
- you have severe or frequent nosebleeds

If pregnant or breast-feeding,

ask a health professional before use.

Keep out of reach of children.

In case of overdose, get medical help or contact a Poison Control Center right away (1-800-222-1222).

Directions

- read the Quick Start Guide for how to:
- prime the bottle
- use the spray
- clean the spray nozzle
- shake gently before each use
- use this product only once a day
- do not use more than directed

ADULTS AND CHILDREN 12 YEARS OF AGE AND OLDER

- Week 1 – use 2 sprays in each nostril once daily
- Week 2 through 6 months – use 1 or 2 sprays in each nostril once daily, as needed to treat your symptoms
- After 6 months of daily use – ask your doctor if you can keep using

CHILDREN 4 TO 11 YEARS OF AGE

- The growth rate of some children may be slower while using this product.
  Children should use for the shortest amount of time necessary to achieve symptom relief. Talk to your child’s doctor if your child needs to use the spray for longer than two months a year.
- an adult should supervise use
- use 1 spray in each nostril daily

CHILDREN UNDER 4 YEARS OF AGE

- do not use

Other information

- you may start to feel relief the first day and full effect after several days of regular, once-a-day use
- store between 4o and 30oC (39o and 86oF)
- keep this package and enclosed materials. They contain important additional information.

Inactive ingredients

benzalkonium chloride, dextrose, microcrystalline cellulose, phenylethyl alcohol, polysorbate 80, purified water, sodium carboxymethylcellulose

Questions or comments?

1-800-719-9260

Consumer Information

FLUTICASONE PROPIONATE NASAL SPRAY QUESTIONS & ANSWERS

WHAT FLUTICASONE PROPIONATE NASAL SPRAY IS, HOW TO USE IT, AND WHAT TO EXPECT.

UNDERSTANDING FLUTICASONE PROPIONATE NASAL SPRAY

What Fluticasone Propionate Nasal Spray is, and how it works.

What is Fluticasone Propionate Nasal Spray?

Fluticasone Propionate Nasal Spray is an effective, allergy medicine that you can buy without a prescription. It works directly in the nose to help block your allergic reactions. Fluticasone Propionate Nasal Spray relieves allergy symptoms caused by pollen, mold, dust and pets.

What is the active ingredient in Fluticasone Propionate Nasal Spray?

The active ingredient in Fluticasone Propionate Nasal Spray is called fluticasone propionate. Fluticasone propionate is a glucocorticoid – a substance produced naturally by your body to help fight inflammation. It works in your nose to relieve your allergy symptoms. Barely any of it travels through your body. It’s been prescribed by doctors for over 20 years, and used effectively by millions.

A glucocorticoid is a kind of steroid that is different from the anabolic (muscle-building) steroids sometimes misused by athletes. In fact, world class athletes are allowed to use glucocorticoids during competition to treat their allergies.

Who should not use Fluticasone Propionate Nasal Spray?

For complete guidance, check the Drug Facts label on the back of the Fluticasone Propionate Nasal Spray package.

Can I use Fluticasone Propionate Nasal Spray for asthma?

No, Fluticasone Propionate Nasal Spray is not a treatment for asthma. Ask your doctor what medicine to take for your asthma.

Can I use Fluticasone Propionate Nasal Spray for colds?

No, use Fluticasone Propionate Nasal Spray to treat only your allergies – not your cold symptoms. If you’re not sure whether your symptoms come from allergies or a cold, ask your doctor.

What happens when you have allergies?

Allergies start when allergens like pollen or pet dander enter your body and trigger your immune system to respond.

Your body’s natural response is to release multiple inflammatory substances, (also referred to as mediators) that cause your allergy symptoms.

How does Fluticasone Propionate Nasal Spray work?

Fluticasone Propionate Nasal Spray works right in your nose to help block your allergic reaction at the source to relieve the symptoms that make you uncomfortable.

Fluticasone Propionate Nasal Spray acts on multiple inflammatory substances, including histamine, prostaglandins, cytokines, tryptases, chemokines and leukotrienes.

Most common OTC allergy pills act on histamine alone.

Because of the way it works, it may take several days for Fluticasone Propionate Nasal Spray to reach maximum effect. That’s why it’s best to use Fluticasone Propionate Nasal Spray regularly, once a day.

Fluticasone Propionate Nasal Spray not only relieves sneezing, itchy nose, runny nose and itchy, watery eyes, but also relieves nasal congestion.

Who should not use Fluticasone Propionate Nasal Spray or check with a doctor first?

Some people should not use Fluticasone Propionate Nasal Spray, or need to check with a health professional first. This table offers a quick summary of these situations.

If you… | Here’s what to do…
Are younger than 4 | Do not use Fluticasone Propionate Nasal Spray
Are pregnant or breast-feeding | Talk to a health professional before using Fluticasone Propionate Nasal Spray
Have or had glaucoma or cataracts | Talk to your doctor before using Fluticasone Propionate Nasal Spray
Have an injury or surgery to your nose that is not fully healed | Do not use Fluticasone Propionate Nasal Spray
Have ever had an allergic reaction to Fluticasone Propionate Nasal Spray or any of its ingredients | Do not use Fluticasone Propionate Nasal Spray
Are taking a medicine for HIV infection (such as ritonavir) | Talk to your doctor or pharmacist before using Fluticasone Propionate Nasal Spray
Are taking ketoconazole pills (medicine for fungal infection) | Talk to your doctor or pharmacist before using Fluticasone Propionate Nasal Spray
Are using a steroid medicine for asthma, allergies, skin rash, allergic reactions, inflammation or eye conditions | Talk to your doctor or pharmacist before using Fluticasone Propionate Nasal Spray

What problems can Fluticasone Propionate Nasal Spray help with?

Allergies can cause uncomfortable symptoms like congestion and itchy eyes. These symptoms can be triggered by allergens like pollen, mold, dust or pet dander.

Fluticasone Propionate Nasal Spray helps relieve a broad range of symptoms from many allergens.

For example, Fluticasone Propionate Nasal Spray helps with:

Nasal symptoms | Eye symptoms | Outdoor allergens | Animal allergens | Indoor allergens
- Congestion | - Itchy eyes | - Weed pollen | - Cats | - Dust
- Runny nose | - Watery eyes | - Grass pollen | - Dogs | - Dust mites
- Sneezing |  | - Tree pollen |  | - Mold
- Itchy nose |  | - Mold spores

USING FLUTICASONE PROPIONATE NASAL SPRAY

How to get the best results with Fluticasone Propionate Nasal Spray.

Read the Drug Facts label on the back of the package or the Quick Start Guide on the other side for simple directions on using Fluticasone Propionate Nasal Spray.

Watch for purple color - it shows where there is different information for children ages 4-11, compared to users age 12 or older.

If you still have questions about using Fluticasone Propionate Nasal Spray after reading the Quick Start Guide, read this section for answers.

I know how to use a nasal spray. Why do I have to follow the directions?

If you don’t use the spray bottle correctly, you might not get a full dose. Without a full dose each time, you might not get the relief you deserve.

Follow the simple directions in the Quick Start Guide on other side.

If my symptoms go away, should I stop using Fluticasone Propionate Nasal Spray?

You may be tempted to stop using Fluticasone Propionate Nasal Spray when you start to feel better. It’s important you keep using Fluticasone Propionate Nasal Spray daily as long as you’re exposed to allergens that bother you, like pollen, mold, dust or pet dander. This way you’ll keep feeling relief.

If you suffer allergy symptoms only during certain times, like when pollen levels are high, you may stop using Fluticasone Propionate Nasal Spray when that time ends. If you are age 12 or older and need to use daily for longer than 6 months or age 4-11 and need to use for longer than 2 months a year, check with your doctor.

What if I miss a dose by accident?

If you miss a dose, just use your regular dose the next day. Don’t add an extra dose to make up for it.

Can I keep using Fluticasone Propionate Nasal Spray year round?

Some people suffer from allergies all year. If you are age 12 or older and have used Fluticasone Propionate Nasal Spray for six months or age 4-11 and have used for two months a year, check with your doctor to make sure it’s OK to keep using Fluticasone Propionate Nasal Spray daily. In fact, it’s a good idea for anyone with persistent allergies to talk with a doctor every so often about symptoms and medicines.

Can I share my Fluticasone Propionate Nasal Spray?

Do not share a bottle of Fluticasone Propionate Nasal Spray. Sharing the bottle can spread germs, because you insert the nozzle in your nose.

Can I spray Fluticasone Propionate Nasal Spray in my eyes or mouth?

No, Fluticasone Propionate Nasal Spray is meant to work only in your nose to relieve your allergy symptoms, including itchy, watery eyes.

Never spray Fluticasone Propionate Nasal Spray in your eyes or your mouth.

Some decongestants may increase blood pressure. Does Fluticasone Propionate Nasal Spray increase blood pressure?

When used as directed, Fluticasone Propionate Nasal Spray does not increase blood pressure.

Won’t I waste product by priming?

It’s not a waste to prime the pump, because it helps you get a full dose. Getting a full dose is important for getting the relief you deserve. See the Quick Start Guide for when and how to prime the pump.

Don’t worry about running out due to priming. There is enough medicine in the spray bottle to allow for priming sprays plus the number of sprays labeled on the bottle.

Always point the spray bottle away from your face when priming.

How long should a bottle of Fluticasone Propionate Nasal Spray last?

This table shows roughly how long your bottle will last. It assumes you follow the instructions for priming the pump, and that those age 12 or older use two sprays in each nostril every day while children age 4-11 use one spray in each nostril every day.

After you’ve used the number of sprays shown on the label, each spray may not deliver a full dose — even if there is liquid left in the bottle.

If the label says… | The bottle should last age 12+… | The bottle should last age 4-11…
60 sprays | 2 weeks | 4 weeks
72 sprays | 2 weeks | 5 weeks
120 sprays | 4 weeks | 8 weeks
144 sprays | 5 weeks | 10 weeks*; *Check with a doctor if a child 4-11 needs to use longer than 2 months a year

Is Fluticasone Propionate Nasal Spray OK to use with other medicines?

You should tell your doctor about all the medicines you take, including Fluticasone Propionate Nasal Spray. Fluticasone Propionate Nasal Spray can be used with most non-prescription and prescription medicines. However, there are a few medicines to look out for because they may cause the level of Fluticasone Propionate Nasal Spray in your body to become too high.

Just to be safe, check this table to see if you’re taking any of these medicines.

If you’re taking… | Here’s what to do…
Medicines for HIV infection (such as ritonavir) | Talk to your doctor or pharmacist before using Fluticasone Propionate Nasal Spray
Medicines with glucocorticoids Including some medicines for skin rash such as eczema, asthma, inflammation, allergic reactions, or eye conditions | Talk to your doctor or pharmacist before using Fluticasone Propionate Nasal Spray
Ketoconazole Pills for fungal infection | Talk to your doctor or pharmacist before using Fluticasone Propionate Nasal Spray

What are the differences in the way children age 4-11 should use Fluticasone Propionate Nasal Spray?

Children age 4-11 should use a lower dose of Fluticasone Propionate Nasal Spray for a shorter period of time.

Ages | Children 4-11 years of age | Users 12 years of age and older
Dosage | 1 spray in each; nostril once daily | Up to 2 sprays; in each nostril once daily
Duration before checking with a doctor | Up to 2 months of use a year | Up to 6 months of daily use

Why is the use of Fluticasone Propionate Nasal Spray for children age 4-11 limited to 2 months a year before checking with a doctor?

When used long-term, intranasal glucocorticoids like Fluticasone Propionate Nasal Spray may cause the growth rate of some children to be slower. Whether this will affect a child’s ultimate height is not known. As a precaution, children should use for the shortest amount of time necessary to achieve symptom relief. Talk to your child’s doctor if your child needs to use the spray for longer than 2 months a year.

WHAT TO EXPECT

What it’s like to use Fluticasone Propionate Nasal Spray.

How soon will I get relief?

You may start to feel relief the first day you use Fluticasone Propionate Nasal Spray. Keep using it every day, though. It takes several days before Fluticasone Propionate Nasal Spray builds up to full effectiveness.

How long will the relief last?

Fluticasone Propionate Nasal Spray is meant to control your symptoms every day, all day and all night. To help you get this lasting relief, it’s important to use Fluticasone Propionate Nasal Spray regularly, once a day.

Does Fluticasone Propionate Nasal Spray cause a “rebound” effect?

No, Fluticasone Propionate Nasal Spray does not cause a rebound effect.

Some nasal decongestant sprays may cause your nasal passages to swell up even more when you use them too often or for longer than their label says you should (three days). This is sometimes called a “rebound effect.”

Fluticasone Propionate Nasal Spray is a different kind of medicine and does not cause any rebound effect. You can use Fluticasone Propionate Nasal Spray for up to six months if you are age 12 or older or up to two months a year if you are age 4-11 before checking with a doctor.

Will Fluticasone Propionate Nasal Spray make me drowsy?

No, Fluticasone Propionate Nasal Spray does not cause drowsiness. Some allergy medications can cause drowsiness, but Fluticasone Propionate Nasal Spray does not.

Why does Fluticasone Propionate Nasal Spray have a smell?

The light floral scent you may notice comes from one of the important ingredients in the Fluticasone Propionate Nasal Spray formula. No fragrance is added to Fluticasone Propionate Nasal Spray.

What if little or nothing is spraying out?

Try priming the spray bottle. It may take a few pumps to get the dispenser spraying again.

If that doesn’t work, the spray nozzle may be clogged. You can clean it following the directions in the Quick Start Guide on the other side.

What if I feel stinging in my nose, or I sneeze?

Some people may feel a slight stinging, or may sneeze, after spraying Fluticasone Propionate Nasal Spray in their nostrils.

This feeling should go away in a few seconds.

What if I feel or taste the medicine in my throat?

Generally, you can avoid this by taking a shallower breath next time you spray Fluticasone Propionate Nasal Spray into your nostrils. For example, take the kind of breath you would use to smell a flower.

What if I have chicken pox, measles or tuberculosis or come into contact with someone who does?

Stop using Fluticasone Propionate Nasal Spray and ask your doctor.

What if I’m having severe sinus pain?

If you feel severe pain in your face, have thick nasal discharge, or think you may have a sinus infection, stop using Fluticasone Propionate Nasal Spray and see your doctor. Your doctor may want to consider if other medicines are needed.

What if my symptoms aren’t better after one week?

If you have used Fluticasone Propionate Nasal Spray for a week and your allergy symptoms are not getting better, stop use and ask your doctor. You may have an infection.

Does Fluticasone Propionate Nasal Spray have side effects?

Serious side effects are rare with Fluticasone Propionate Nasal Spray because Fluticasone Propionate Nasal Spray works in your nose, and barely any of it travels through your body. However, like all medicines, Fluticasone Propionate Nasal Spray can cause side effects in some people.

Here are some side effects that have been reported when using Fluticasone Propionate Nasal Spray. If you have any concerns about side effects, talk with your doctor.

Side effect | What could happen | What to do
Allergic reaction to the product | - Sudden swelling of face or tongue - A rash - Wheezing or feeling faint | If you feel any of these symptoms, stop using Fluticasone Propionate Nasal Spray and see a doctor right away.
Nose injury | - Severe or frequent nosebleeds | Apply pressure to your nose. Stop using Fluticasone Propionate Nasal Spray and see a doctor.
Nose injury | - Constant whistling sound that does not go away | This could be a sign of damage to your nose. Stop using Fluticasone Propionate Nasal Spray and see a doctor right away.
Eye conditions such as cataracts or glaucoma | - Cloudy vision - Reduced vision | Have a yearly eye exam to check for these conditions. Read the Drug Facts on the back of the Fluticasone Propionate Nasal Spray package for more details.
Growth effects | - Slower growth rate in some children while using product | Talk to your doctor if you are concerned or if a child age 4-11 needs to use Fluticasone Propionate Nasal Spray for longer than two months a year.
Other side effects | - Headaches or sneezing - Bad taste or smell - Minor nosebleeds - Dry or irritated nose or throat. | Talk to your doctor or pharmacist if you are concerned.

STILL HAVE QUESTIONS? Call 1-800-719-9260

FLUTICASONE PROPIONATE NASAL SPRAY

QUICK START GUIDE

HOW TO START GETTING ALLERGY RELIEF RIGHT NOW

USE THE RIGHT DOSE

Fluticasone Propionate Nasal Spray works best when you use it daily. Here’s how to get started.

Children age 4-11

An adult should supervise use

Use one spray in each nostril once daily.

Don’t use more than one spray in each nostril per day.

If you miss a dose, just use your regular dose the next day. Don’t add an extra dose.

Check with a doctor if a child needs to use Fluticasone Propionate Nasal Spray for longer than two months a year.

Users age 12 or older

In your first week

Use two sprays in each nostril every day.

Don’t use more than two sprays in each nostril per day.

After your first week

If your symptoms are under control, you may reduce to one spray in each nostril every day. If your symptoms get worse, go back to two sprays in each nostril.

If you miss a dose, just use your regular dose the next day. Don’t add an extra dose.

WARNING: Do not spray in your eyes. Only for use in your nose.

KEEP IT CLEAN

A clean spray nozzle helps ensure a full dose. Clean it weekly, or if it’s clogged. Don’t try to unblock nozzle with pin or sharp object — that can damage it.

Remove spray nozzle by grasping at base and pulling up.

Rinse under running tap, and dry at room temperature.

Aim away from your face and gently replace spray nozzle until you hear a soft click.

If spray nozzle is clogged, soak in warm water. Then repeat steps 2 and 3.

GET THE RELIEF YOU NEED.

Fluticasone Propionate Nasal Spray can relieve your allergy symptoms. For best results, it’s important to get a full dose.

Here’s how, in five easy steps.

Gently shake spray bottle.

Remove clear cap.

Do this when:

- Starting new bottle
- Haven’t used it in a week
- Just cleaned nozzle

Otherwise go to Step 3.

Aim away from face. Grasp spray bottle as shown. Pump until fine mist appears.

Pumped six times and still no mist? Spray nozzle may be clogged. See KEEP IT CLEAN.

Blow nose gently to clear nostrils.

Close one nostril and put tip of spray nozzle in other nostril.

Put just the tip into your nose.

Aim slightly away from center of nose.

While sniffing gently, press down on spray nozzle once or twice (according to dosing instructions). You’ll feel a light mist in your nose. Breathe out through your mouth.

Repeat in other nostril.

Wipe spray nozzle with clean tissue and replace cap.

Distributed By

Perrigo®

Allegan, MI 49010

1G700 00 J6

Package/Label Principal Display Panel

VALUE PACK

3 BOTTLES OF 144 METERED SPRAYS

CVS Health®

Compare to the active ingredient in Flonase® Allergy Relief

Full Prescription Strength | Non-Drowsy

Fluticasone Propionate (Glucocorticoid), 50 mcg per spray

ALLERGY SYMPTOM RELIEVER NASAL SPRAY

24 Hour relief of:

● Itchy, watery eyes ● Itchy nose

● Nasal congestion ● Sneezing

● Runny nose

24 HOUR RELIEF

Allergy Relief

3 X 120 METERED SPRAYS

3 X 144 METERED SPRAYS

3 BOTTLES - 0.62 FL OZ (18.2 mL) EACH

1.86 FL OZ (54.6 mL) TOTAL

Actual Bottle Size on Side Panel